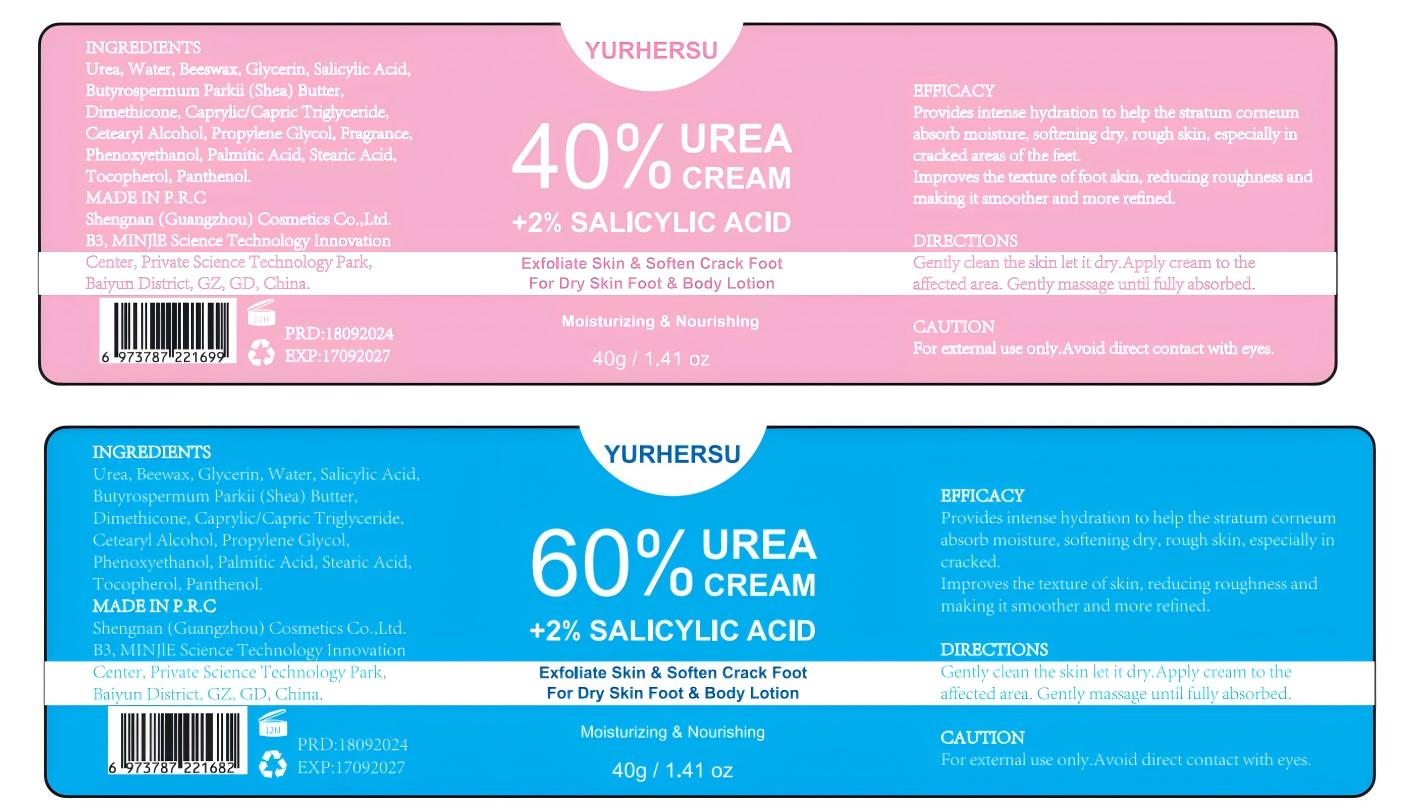 DRUG LABEL: UreaCream
NDC: 84019-009 | Form: CREAM
Manufacturer: Shengnan (Guangzhou) Cosmetics Co., LTD
Category: otc | Type: HUMAN OTC DRUG LABEL
Date: 20241118

ACTIVE INGREDIENTS: 1,3-BIS(BENZOTHIAZOL-2-YLTHIOMETHYL)UREA 100 mg/1 g
INACTIVE INGREDIENTS: CAPRYLIC/CAPRIC TRIGLYCERIDE; FRAGRANCE 13576; TOCOPHEROL; SALICYLIC ACID; BEESWAX; BUTYROSPERMUM PARKII (SHEA) BUTTER; WATER; DIMETHICONE; GLYCERIN; PROPYLENE GLYCOL 1-(2-METHYLBUTYRATE); STEARIC ACID; CETEARYL ALCOHOL; PALMITIC ACID; PHENOXYETHANOL; PANTHENOL

UREA CREAM

WARNINGS

For externnl use only.Avoid direct contact with eyes

PURPOSE

Improves the texture of foot akin, reduicing roughness and making it smoother and more refined.

USE SECTION

Stop use and ask doctor if rash occurs.

ACTIVE INGREDIENT

Urea 40%

WHEN USING SECTION

Do not apply to wounds or damaged skin

INACTIVE INGREDIENT

Water
Beeswax

Glycerin

Salicylic Acid

Butyrospermum Parkii （Shea） Butter
Dimethicone

Caprylic/Capric Triglyceride
Cetearyl Alcohol

Propylene Glycol
Fragrance
Phenoxyethanol
Palmitic Acid

Stearic Acid
Tocopherol
Panthenol

DOSAGE AND ADMINISTRATION

Apply 1-2 times a day

INDICATIONS AND USAGE

Gently clean the slin let it dry.Apply cream to theafected area. Gendy massage until fullyabsorbed